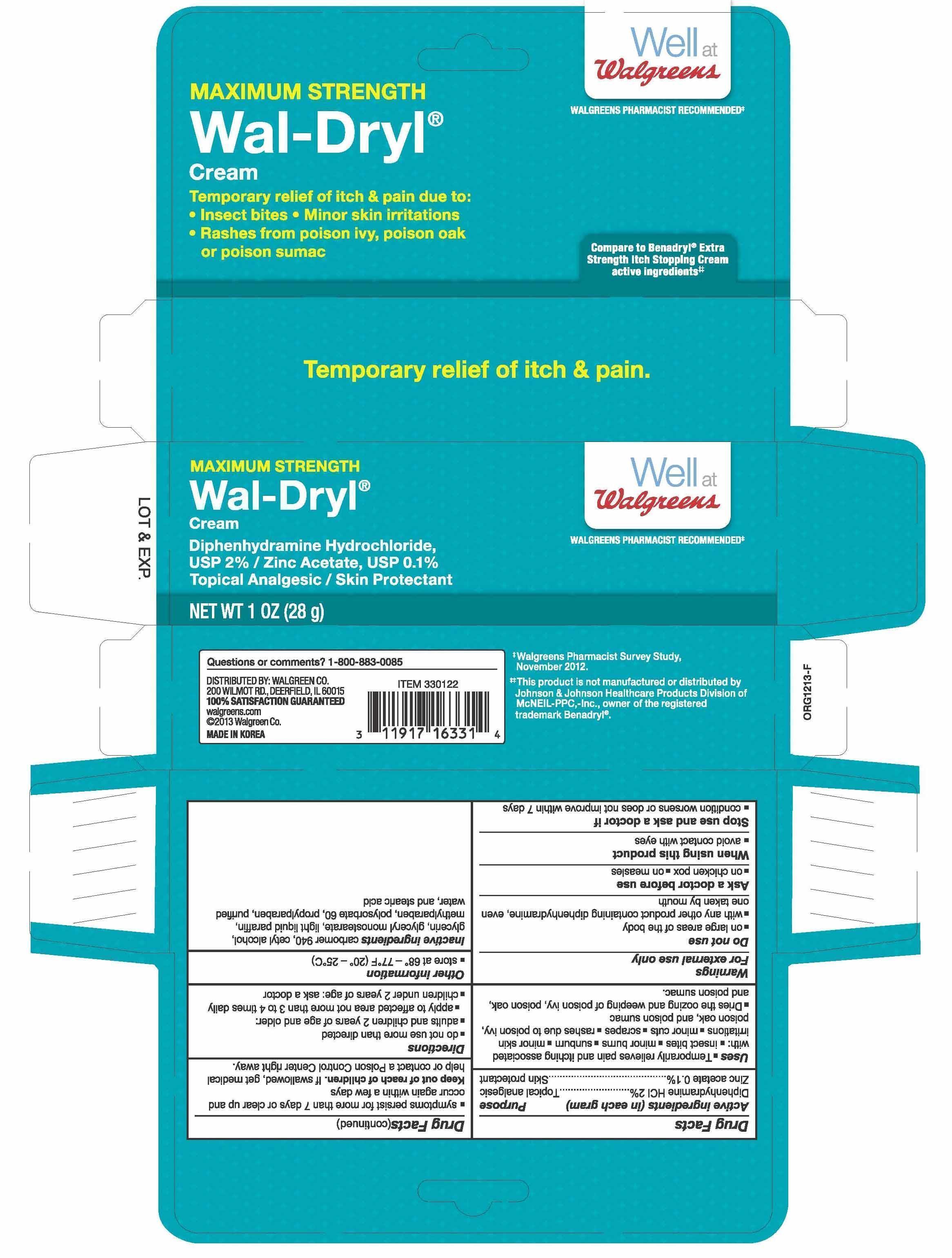 DRUG LABEL: Wal-dryl
NDC: 0363-0122 | Form: CREAM
Manufacturer: Walgreen Company
Category: otc | Type: HUMAN OTC DRUG LABEL
Date: 20140327

ACTIVE INGREDIENTS: DIPHENHYDRAMINE HYDROCHLORIDE 2 mg/1 g; ZINC ACETATE 0.1 mg/1 g
INACTIVE INGREDIENTS: CARBOMER 940; CETYL ALCOHOL; GLYCERIN; GLYCERYL MONOSTEARATE; PARAFFIN; METHYLPARABEN; POLYSORBATE 60; PROPYLPARABEN; WATER; STEARIC ACID

Allergy Cream with Zinc Acetate

ACTIVE INGREDIENT

Diphenhydramine hydrochloride, USP 2%

Zinc acetate, USP 0.1%

PURPOSE

Topical analgesic

Skin protectant

USES

For the temporary relief of pain and itching associated with

- minor burns
- sunburn
- minor cuts
- scrapes
- insect bites
- minor skin irritations
- rashes due to poison ivy, oak and sumac
- dries the oozing and weeping of poison:
  - ivy
  - oak
  - sumac

WARNINGS

For external use only

DO NOT USE

- on large areas of the body
- with any other product containing diphenhydramine, even one taken by mouth

ASK A DOCTOR BEFORE USE

- on chicken pox
- on measles

WHEN USING THIS PRODUCT

- avoid contact with the eyes

STOP USE AND ASK A DOCTOR IF

- condition gets worse
- symptoms persist for more than 7 days or clear up and occur again within a few days

KEEP OUT OF REACH OF CHILDREN

If swallowed, get medical help or contact a Poison Control Center right away.

DIRECTIONS

- do not use more often than directed
- adults and children 2 years of age and older: apply to affected area not more than 3 to 4 times daily
- children under 2 years of age: ask a doctor

OTHER INFORMATION

- Store between 59°-86°F (15°-30°C).

INACTIVE INGREDIENT

cetyl alcohol, methylparaben, polysorbate 60, propylene glycol, purified water, sorbitan monostearate

PACKAGE LABEL.PRINCIPAL DISPLAY PANEL

NDC 0363-0525-56

Walgreens The Brand America Trusts®

Compare to the active ingredients in BENADRYL® EXTRA STRENGTH ITCH STOPPING CREAM*

Wal-dryl

Topical Analgesic/Skin Protectant

ITCH RELIEF

MAXIMUM STRENGTH

2% Diphenhydramine Hydrochloride, USP and 0.1% Zinc Acetate, USP

Temporary Relief of Itch and Pain due to

• Insect Bites • Minor Skin Irritations •Rashes from Poison Ivy, Poison Oak or Poison Sumac

PHARMACIST RECOMMENDED

NET WT. 1 OZ (28 g)

05250111F1 VC110348

*This product is not affiliated with, manufactured by, or produced by the makers or owners of Benadryl®.

Made in USA

Distributed by: Walgreen Co.,

200 Wilmot Rd., Deerfield, IL 60015-4616

Quality Guaranteed

100% Satisfaction Guaranteed with all Walgreens Products or Your Money Back. www.walgreeens.com